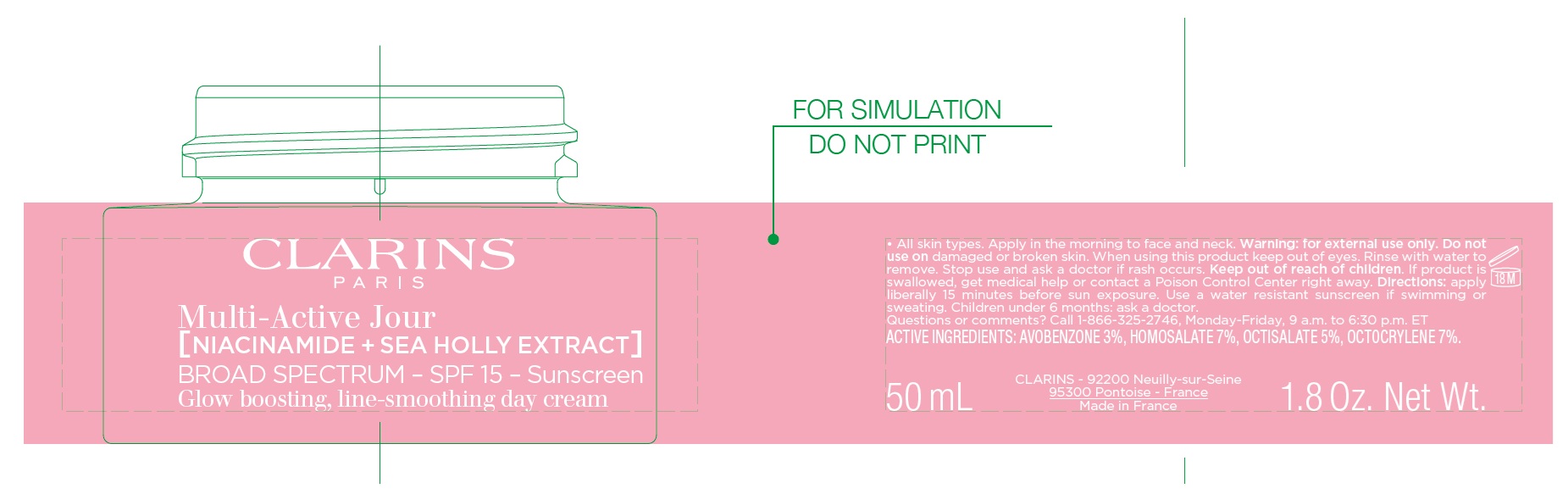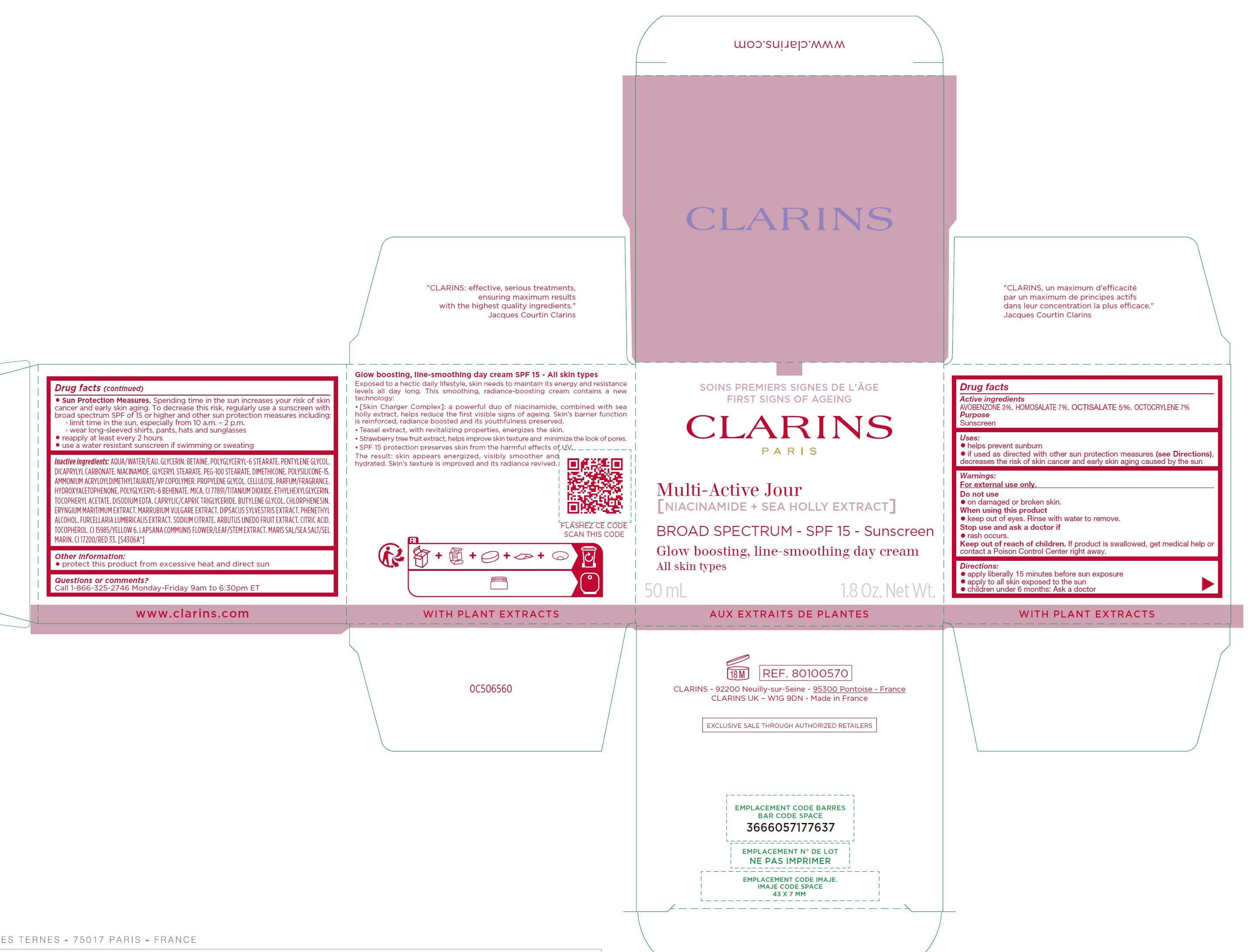 DRUG LABEL: CLARINS Multi-Active Jour Niacinamide and Sea Holly Extract Sunscreen SPF 15
NDC: 58668-9621 | Form: CREAM
Manufacturer: Laboratoires Clarins
Category: otc | Type: HUMAN OTC DRUG LABEL
Date: 20250407

ACTIVE INGREDIENTS: AVOBENZONE 30 mg/1 mL; HOMOSALATE 70 mg/1 mL; OCTISALATE 50 mg/1 mL; OCTOCRYLENE 70 mg/1 mL
INACTIVE INGREDIENTS: WATER; GLYCERIN; BETAINE; POLYGLYCERYL-6 STEARATE; PENTYLENE GLYCOL; DICAPRYLYL CARBONATE; NIACINAMIDE; GLYCERYL STEARATE; PEG-100 STEARATE; DIMETHICONE; POLYSILICONE-15; AMMONIUM ACRYLOYLDIMETHYLTAURATE/VP COPOLYMER; PROPYLENE GLYCOL; POWDERED CELLULOSE; HYDROXYACETOPHENONE; POLYGLYCERYL-6 BEHENATE; MICA; TITANIUM DIOXIDE; ETHYLHEXYLGLYCERIN; .ALPHA.-TOCOPHEROL ACETATE; EDETATE DISODIUM; MEDIUM-CHAIN TRIGLYCERIDES; BUTYLENE GLYCOL; CHLORPHENESIN; HOREHOUND; PHENYLETHYL ALCOHOL; FURCELLERAN; SODIUM CITRATE, UNSPECIFIED FORM; ARBUTUS UNEDO FRUIT; CITRIC ACID MONOHYDRATE; TOCOPHEROL; FD&C YELLOW NO. 6; LAPSANA COMMUNIS FLOWERING TOP; SEA SALT; D&C RED NO. 33

CLARINS - Multi-Active Jour Niacinamide & Sea Holly Extract Sunscreen SPF 15

Active ingredients

AVOBENZONE 3%. HOMOSALATE 7%. OCTISALATE 5%. OCTOCRYLENE 7%

Purpose

Sunscreen

Uses:

- helps prevent sunburn
- if used as directed with other sun protection measures (see Directions),decreases the risk of skin cancer and early skin aging caused by the sun

Warnings:

For external use only.

Do not use

- on damaged or broken skin.

When using this product

- keep out of eyes. Rinse with water to remove.

Stop use and ask a doctor if

- rash occurs.

Keep out of reach of children.

If product is swallowed, get medical help or contact a Poison Control Center right away.

Directions:

- apply liberally 15 minutes before sun exposure
- apply to all skin exposed to the sun
- children under 6 months: Ask a doctor
- Sun Protection Measures.Spending time in the sun increases your risk of skin cancer and early skin aging. To decrease this risk, regularly use a sunscreen with broad spectrum SPF of 15 or higher and other sun protection measures including:
- limit time in the sun, especially from 10 a.m. – 2 p.m.
- wear long-sleeved shirts, pants, hats and sunglasses
- reapply at least every 2 hours
- use a water resistant sunscreen if swimming or sweating

Inactive ingredients:

AQUA/WATER. GLYCERIN. BETAINE. POLYGLYCERYL-6 STEARATE. PENTYLENE GLYCOL. DICAPRYLYL CARBONATE. NIACINAMIDE. GLYCERYL STEARATE. PEG-100 STEARATE. DIMETHICONE. POLYSILICONE-15. AMMONIUM ACRYLOYLDIMETHYLTAURATE/VP COPOLYMER. PROPYLENE GLYCOL. CELLULOSE. PARFUM/FRAGRANCE. HYDROXYACETOPHENONE. POLYGLYCERYL-6 BEHENATE. MICA. CI 77891/TITANIUM DIOXIDE. ETHYLHEXYLGLYCERIN. TOCOPHERYL ACETATE. DISODIUM EDTA. CAPRYLIC/CAPRIC TRIGLYCERIDE. BUTYLENE GLYCOL. CHLORPHENESIN. ERYNGIUM MARITIMUM EXTRACT. MARRUBIUM VULGARE EXTRACT. DIPSACUS SYLVESTRIS EXTRACT. PHENETHYL ALCOHOL. FURCELLARIA LUMBRICALIS EXTRACT. SODIUM CITRATE. ARBUTUS UNEDO FRUIT EXTRACT. CITRIC ACID. TOCOPHEROL. CI 15985/YELLOW 6. LAPSANA COMMUNIS FLOWER/LEAF/STEM EXTRACT. MARIS SAL/SEA SALT/SEL MARIN. CI 17200/RED 33. [S4306A*]

Other Information:

- protect this product from excessive heat and direct sun

Questions or comments?

Call 1-866-325-2746 Monday-Friday 9am to 6:30pm ET www.clarins.com